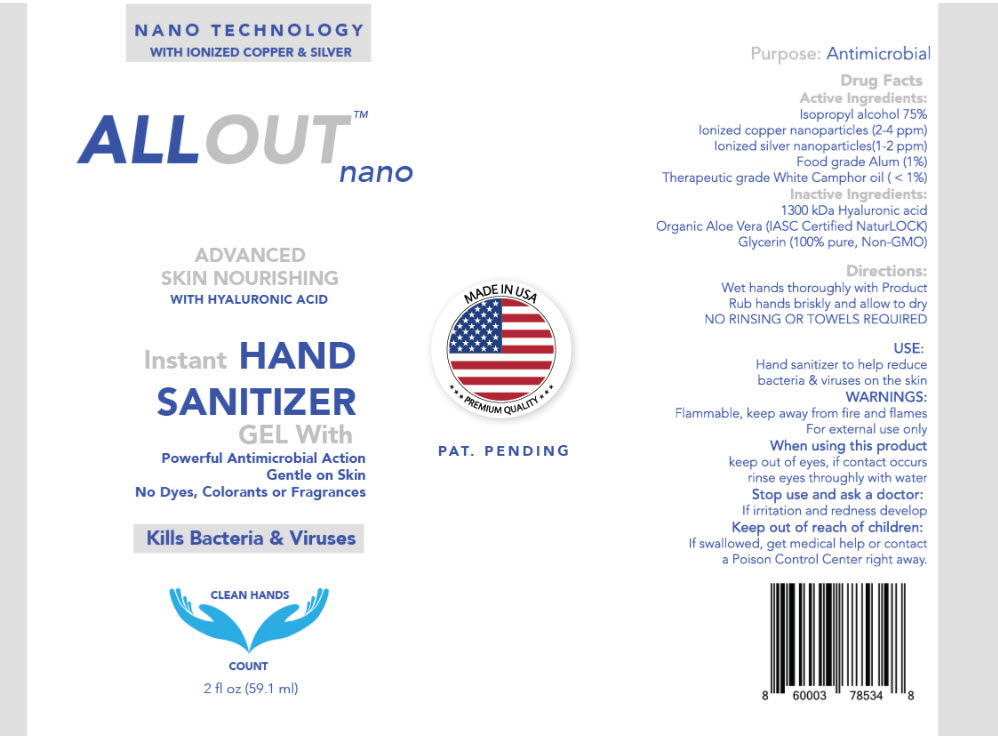 DRUG LABEL: Hand Sanitizer
NDC: 75814-102 | Form: GEL
Manufacturer: SERENITY TECHNOLOGIES INC.
Category: otc | Type: HUMAN OTC DRUG LABEL
Date: 20200504

ACTIVE INGREDIENTS: ISOPROPYL ALCOHOL 750 mL/1000 mL; COPPER 3 mg/1000 mL; SILVER 1.5 mg/1000 mL; POTASSIUM ALUM 100 mg/1000 mL; CAMPHOR OIL, WHITE 9 g/1000 mL
INACTIVE INGREDIENTS: Water; hyaluronic acid; glycerin

Hand Sanitizer

Drug Facts

Active Ingredients

Isopropyl Alcohol (700 mL/L)

Ionized Copper Nanoparticles 40-60 nm (2-4 ppm)

Ionized Silver Nanoparticles 5 nm (1-2 ppm)

Food grade Alum (1% vol)

White Camphor Oil (< 1% vol)

Purpose

Antimicrobial

Use

Hand sanitizer to help reduce bacteria and viruses on the skin

Warnings

Flammable, keep away from fire and flames. For external use only

When using this product

- Keep out of eyes
- If contact occurs, rinse eyes throughly with water

Stop use and a doctor if

- irritation and redness develop

Keep out of reach of children.

If swallowed, get medical help or contact a Poison Control Center right away

Directions

wet hands thoroughly with product, rub hands briskly and allow to dry. No rinsing or towels required.

Inactive Ingredients

Water, hyaluronic acid, aloe barbadensis, glycerine

PRINCIPAL DISPLAY PANEL - 59.1 ml Bottle Label

NANO TECHNOLOGY
WITH IONIZED COPPER & SILVER

ALLOUT™
nano

ADVANCED
SKIN NOURISHING
WITH HYALURONIC ACID

Instant HAND
SANITIZER
GEL With
Powerful Antimicrobial Action
Gentle on Skin
No Dyes, Colorants or Fragrances

Kills Bacteria & Viruses

CLEAN HANDS

COUNT

2 fl oz (59.1 ml)